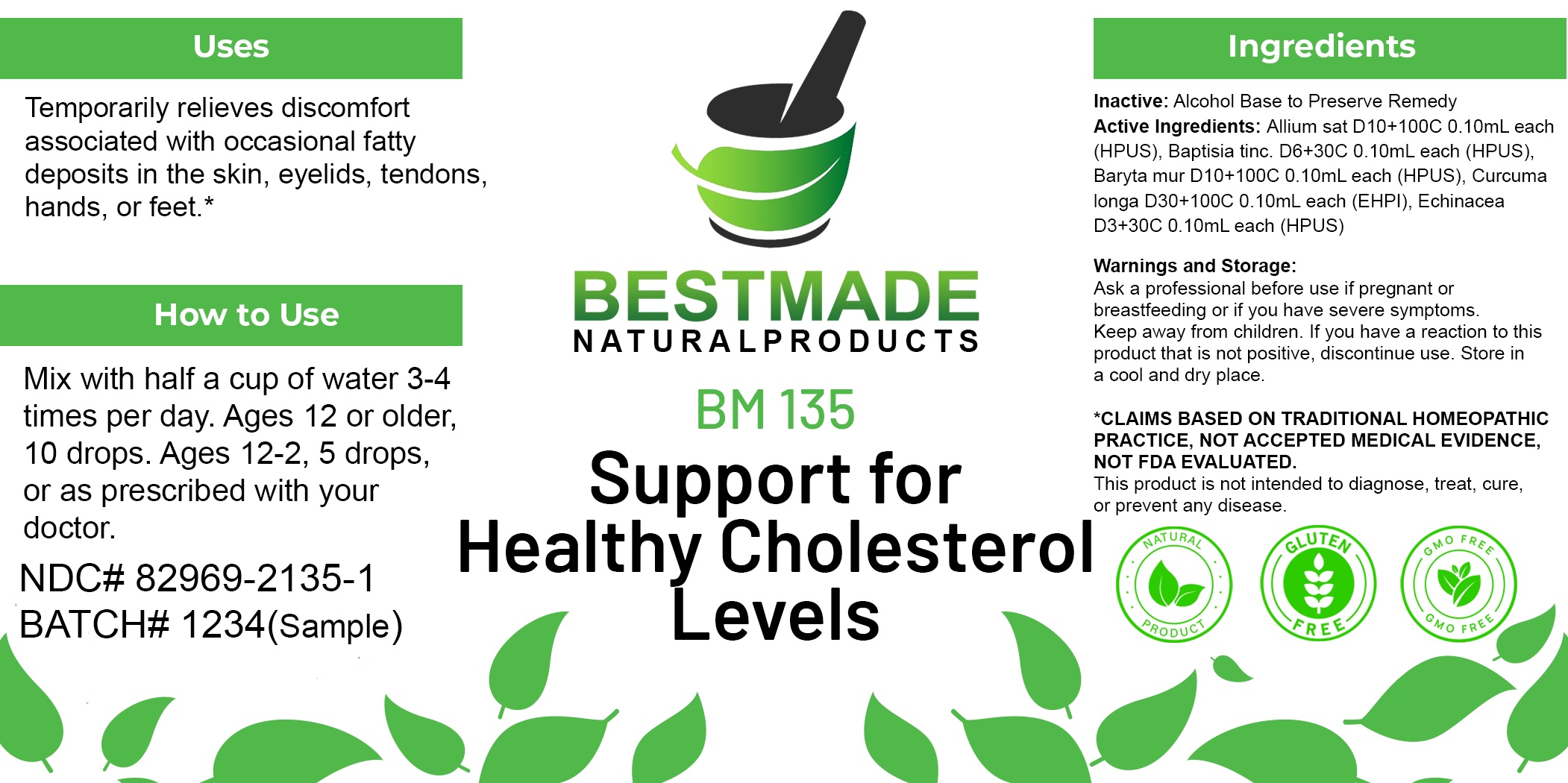 DRUG LABEL: Bestmade Natural Products BM135
NDC: 82969-2135 | Form: LIQUID
Manufacturer: Bestmade Natural Products
Category: homeopathic | Type: HUMAN OTC DRUG LABEL
Date: 20250212

ACTIVE INGREDIENTS: ECHINACEA ANGUSTIFOLIA WHOLE 30 [hp_C]/30 [hp_C]; BAPTISIA TINCTORIA ROOT 30 [hp_C]/30 [hp_C]; BARIUM CHLORIDE DIHYDRATE 30 [hp_C]/30 [hp_C]; TURMERIC 30 [hp_C]/30 [hp_C]; GARLIC 30 [hp_C]/30 [hp_C]
INACTIVE INGREDIENTS: ALCOHOL 30 [hp_C]/30 [hp_C]

BM135

DOSAGE AND ADMINISTRATION

How to Use

Mix with half a cup of water 3-4 times per day. Ages 12 or older, 10 drops. Ages 12-2, 5 drops. Ages 2 and under, consult your Doctor.

Inactive:

Alcohol Base to Preserve Product

ACTIVE INGREDIENTS

Allium sat D10+100C 0.10mL each (HPUS), Baptisia tinc. D6+30C 0.10mL each (HPUS), Baryta mur D10+100C 0.10mL each (HPUS), Curcuma longa D30+100C 0.10mL each (EHPI), Echinacea D3+30C 0.10mL each (HPUS)

Uses
Temporarily relieves discomfort associated with occasional fatty deposits in the skin, eyelids, tendons, hands, or feet.*

Uses
Temporarily relieves discomfort associated with occasional fatty deposits in the skin, eyelids, tendons, hands, or feet.*

KEEP OUT OF REACH OF CHILDREN

Warnings and Storage:

Ask a professional before use if pregnant or breastfeeding or if you have severe symptoms.

Keep away from children. If you have a reaction to this product that is not positive, discontinue use. Store in a cool and dry place

*CLAIMS BASED ON TRADITIONAL HOMEOPATHIC PRACTICE, NOT ACCEPTED MEDICAL EVIDENCE NOT FDA EVALUATED.
This product is not intended to diagnose, treat, cure, or prevent any disease.

Warnings and Storage:

Ask a professional before use if pregnant or breastfeeding or if you have severe symptoms.

Keep away from children. If you have a reaction to this product that is not positive, discontinue use. Store in a cool and dry place

*CLAIMS BASED ON TRADITIONAL HOMEOPATHIC PRACTICE, NOT ACCEPTED MEDICAL EVIDENCE NOT FDA EVALUATED.
This product is not intended to diagnose, treat, cure, or prevent any disease.

Entire package label